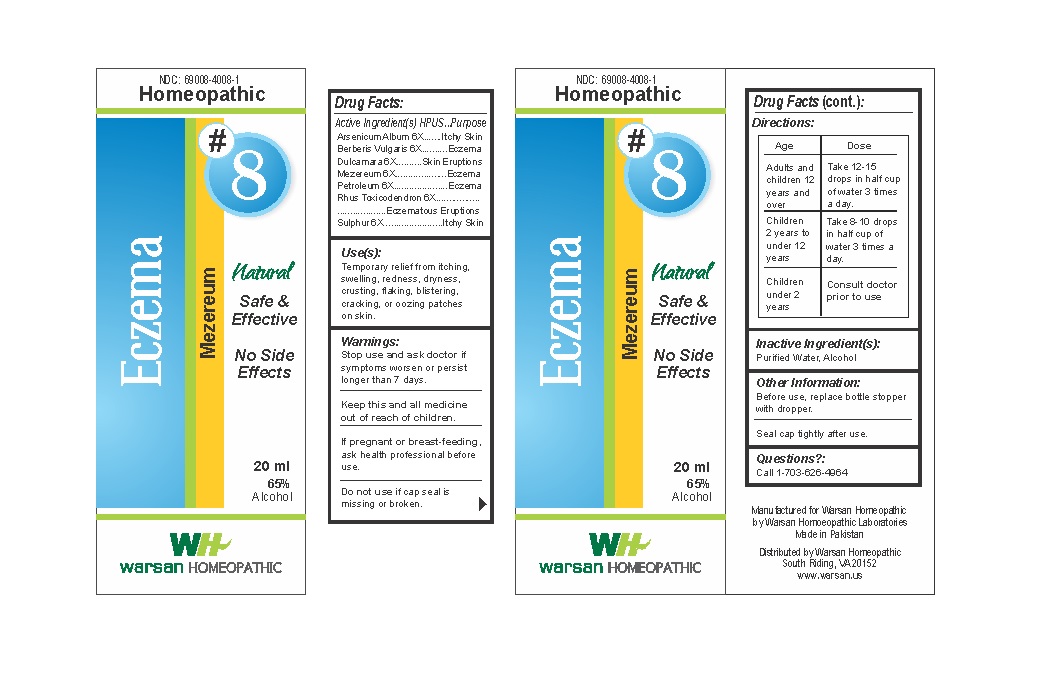 DRUG LABEL: Combination Remedy 8 - Eczema
NDC: 69008-4008 | Form: SOLUTION/ DROPS
Manufacturer: Warsan Homoeopathic Laboratories
Category: homeopathic | Type: HUMAN OTC DRUG LABEL
Date: 20171225

ACTIVE INGREDIENTS: SOLANUM DULCAMARA TOP 6 [hp_X]/1 mL; ARSENIC TRIOXIDE 6 [hp_X]/1 mL; KEROSENE 6 [hp_X]/1 mL; TOXICODENDRON PUBESCENS LEAF 6 [hp_X]/1 mL; BERBERIS VULGARIS ROOT BARK 6 [hp_X]/1 mL; DAPHNE MEZEREUM BARK 6 [hp_X]/1 mL; SULFUR 6 [hp_X]/1 mL
INACTIVE INGREDIENTS: ALCOHOL; WATER

Stop use and ask doctor if symptoms worsen or persist longer than 7 days.

If pregnant or breast-feeding, ask health professional before use.

Do not use if tamper evident seal is missing or broken.

Keep out of reach of children.

ACTIVE INGREDIENT

Arsenicum Album 6X

Berberis Vulgaris 6X

Dulcamara 6X

Mezereum 6X

Petroleum 6X

Rhus Toxicodendron 6X

Sulphur 6X

PURPOSE

Temporary relief from itching, swelling, redness, dryness, crusting, flaking, blistering, cracking, or oozing patches on skin.

INACTIVE INGREDIENT

Purified Water

Alcohol

DOSAGE AND ADMINISTRATION

Adults and children 12 years and older: Take 10-15 drops in half cup of water 3 times a day.

Children 2 years to under 12 years: Take 8-10 drops in half cup of water of 3 times a day.

Children under 2 years: Consult doctor prior to use.

INDICATIONS AND USAGE

Temporary relief from itching, swelling, redness, dryness, crusting, flaking, blistering, cracking, or oozing patches on skin.